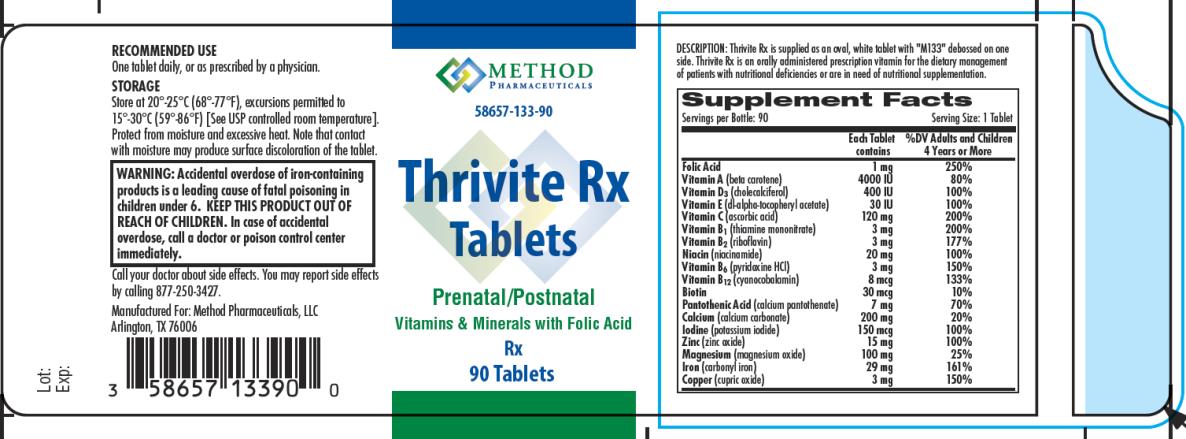 DRUG LABEL: Thrivite Rx
NDC: 58657-133 | Form: TABLET
Manufacturer: Method Pharmaceuticals, LLC
Category: other | Type: DIETARY SUPPLEMENT
Date: 20150820

ACTIVE INGREDIENTS: FOLIC ACID 1 mg/1 1; .BETA.-CAROTENE 4000 [iU]/1 1; CHOLECALCIFEROL 400 [iU]/1 1; .ALPHA.-TOCOPHEROL ACETATE, DL- 30 [iU]/1 1; ASCORBIC ACID 120 mg/1 1; THIAMINE MONONITRATE 3 mg/1 1; RIBOFLAVIN 3 mg/1 1; NIACINAMIDE 20 mg/1 1; PYRIDOXINE HYDROCHLORIDE 3 mg/1 1; CYANOCOBALAMIN 8 ug/1 1; BIOTIN 30 ug/1 1; CALCIUM PANTOTHENATE 7 mg/1 1; CALCIUM CARBONATE 200 mg/1 1; POTASSIUM IODIDE 150 ug/1 1; ZINC OXIDE 15 mg/1 1; MAGNESIUM OXIDE 100 mg/1 1; IRON 29 mg/1 1; CUPRIC OXIDE 3 mg/1 1
INACTIVE INGREDIENTS: CELLULOSE, MICROCRYSTALLINE; HYPROMELLOSES; TITANIUM DIOXIDE; POLYVINYL ALCOHOL; POLYETHYLENE GLYCOLS; TALC; CROSCARMELLOSE SODIUM; MAGNESIUM STEARATE; STEARIC ACID; SILICON DIOXIDE

Thrivite Rx

STATEMENT OF IDENTITY:

Thrivite Rx is an orally administered prescription dietary supplement and should be administered under the supervision of a licensed medical practitioner.

WARNING:

Accidental overdose of iron-containing products is a leading cause of fatal poisoning in children under 6. Keep this product out of reach of children. In case of accidental overdose, call a doctor or poison control center immediately.

DOSAGE AND ADMINISTRATION:

One tablet daily, or as prescribed by a physician.

Supplement Facts

Servings per Bottle: 90 Serving Size: 1 Tablet

Each Tablet %DV Adults and Children contains 4 Years or More

Folic Acid 1 mg 250%

Vitamin A (beta carotene) 4000 IU 80%

Vitamin D3 (cholecalciferol) 400 IU 100%

Vitamin E

(dl-alpha-tocopheryl acetate) 30 IU 100%

Vitamin C (ascorbic acid) 120 mg 200%

Vitamin B1 (thiamine mononitrate) 3 mg 200%

Vitamin B2 (riboflavin) 3 mg 177%

Niacin (niacinamide) 20 mg 100%

Vitamin B6 (pyridoxine HCl) 3 mg 150%

Vitamin B12 (cyanocobalamin) 8 mcg 133%

Biotin 30 mcg 10%

Pantothenic Acid (calcium pantothenate) 7 mg 70%

Calcium (calcium carbonate) 200 mg 20%

Iodine (potassium iodide) 150 mcg 100%

Zinc (zinc oxide) 15 mg 100%

Magnesium (magnesium oxide) 100 mg 25%

Iron (carbonyl iron) 29 mg 161%

Copper (cupric oxide) 3 mg 150%

ALSO CONTAINS: Microcrystalline Cellulose, Pregelatinized Starch, Hypromellose, Titanium Dioxide, Polyvinyl Alcohol, Polyethylene Glycol, Talc, Croscarmellose Sodium, Magnesium Stearate, Stearic Acid, Fumed Silica.

HOW SUPPLIED: Thrivite Rx is supplied as an oval, white tablet with "M133" debossed on one side. Thrivite Rx is dispensed in bottles of 90 tablets.

PRECAUTIONS/WARNING:

PRECAUTIONS

General: Folic acid, when prescribed as a single agent in doses above 0.1 mg daily, may obscure the detection of B12 deficiency (specifically, the administration of folic acid may reverse the hematological manifestations of B12 deficiency, including pernicious anemia, while not addressing the neurological manifestations). Reduced folates may be less likely than folic acid to mask vitamin B12 deficiency. Folate therapy alone is inadequate for the treatment of B12 deficiency.

STORAGE: Store at 20°-25° C (68°-77° F). Excursions permitted to 15°-30° C (59°-86° F). [See USP Controlled

Room Temperature]. Protect from light and moisture. Dispense in a tight, light-resistant container.

HEALTH CLAIMS:

Prescription Vitamin B9 Containing Dietary Supplement

PRINCIPAL DISPLAY PANEL

NDC 58657-133-90
Thrivite Rx
Tablets
Rx
90 Tablets